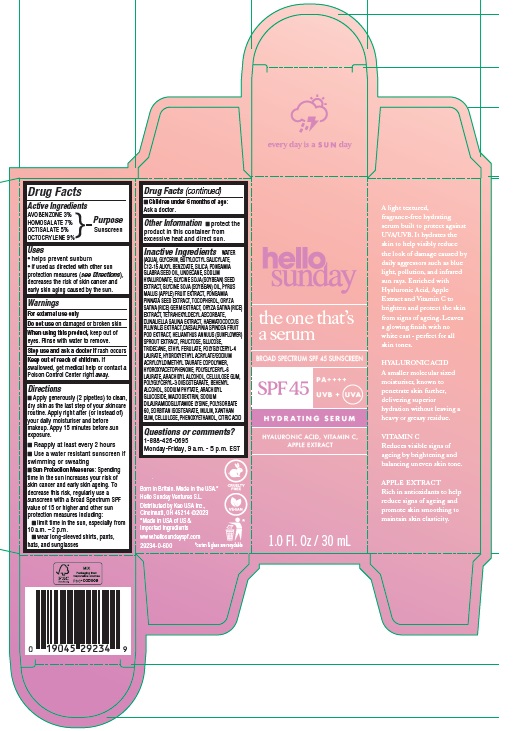 DRUG LABEL: Hello Sunday The One Thats a Serum Hydrating Serum SPF 45
NDC: 10596-803 | Form: EMULSION
Manufacturer: Kao USA Inc.
Category: otc | Type: HUMAN OTC DRUG LABEL
Date: 20250131

ACTIVE INGREDIENTS: OCTISALATE 50 mg/1 mL; OCTOCRYLENE 90 mg/1 mL; HOMOSALATE 70 mg/1 mL; AVOBENZONE 30 mg/1 mL
INACTIVE INGREDIENTS: POLYSORBATE 60; ANHYDROUS DEXTROSE; POLYGLYCERYL-4 LAURATE; SORBITAN ISOSTEARATE; HYALURONATE SODIUM; ARACHIDYL GLUCOSIDE; BUTYLOCTYL SALICYLATE; MALTODEXTRIN; WATER; RICE GERM; GLYCERIN; ETHYL FERULATE; TETRAHEXYLDECYL ASCORBATE; CAESALPINIA SPINOSA FRUIT POD; HELIANTHUS ANNUUS SPROUT; PHYTATE SODIUM; HYDROXYACETOPHENONE; KARUM SEED OIL; UNDECANE; ALKYL (C12-15) BENZOATE; XANTHAN GUM; SOYBEAN; APPLE; PONGAMIA PINNATA SEED; TOCOPHEROL; POLYGLYCERYL-3 DIISOSTEARATE; DUNALIELLA SALINA; SOYBEAN OIL; HAEMATOCOCCUS PLUVIALIS; SILICON DIOXIDE; FRUCTOSE; CITRIC ACID MONOHYDRATE; POWDERED CELLULOSE; HYDROXYETHYL ACRYLATE/SODIUM ACRYLOYLDIMETHYL TAURATE COPOLYMER (45000 MPA.S AT 1%); POLYGLYCERYL-6 LAURATE; INULIN; PHENOXYETHANOL; CARBOXYMETHYLCELLULOSE SODIUM, UNSPECIFIED FORM; DOCOSANOL; SODIUM DILAURAMIDOGLUTAMIDE LYSINE; ARACHIDYL ALCOHOL; TRIDECANE

Hello Sunday The One That's a Serum Hydrating Serum SPF 45

Active Ingredients

AVOBENZONE 3%
HOMOSALATE 7%
OCTISALATE 5%
OCTOCRYLENE 9%

Purpose

Sunscreen

Uses

- helps prevent sunburn
- if used as directed with other sun protection measures (see Directions), decreases the risk of skin cancer and early skin ageing caused by the sun.

Warnings

For external use only

Do not use

on damaged or broken skin

Stop use and ask a doctor if

rash occurs

When using this product

keep out of eyes. Rinse with water to remove.

Keep out of reach of children.

If swallowed, get medical help or contact a Poison Control Center right away.

Directions

- Apply generously (2 pipettes) to clean, dry skin as the last step of your skincare routine. Apply right after (or instead of) your daily moisturiser and before makeup. Appy 15 minutes before sun exposure.
- Reapply at least every 2 hours.
- Use a water resistant sunscreen if swimming or sweating
- Sun Protection Measures: Spending time in the sun increases your risk of skin cancer and early skin ageing. To decrease this risk, regularly use a sunscreen with a Broad Spectrum SPF value of 15 or higher and other sun protection measures including:
- limit time in the sun, especially from 10 a.m. – 2 p.m.
- wear long-sleeved shirts, pants, hats, and sunglasses
- Children under 6 months of age: Ask a doctor.

Other Information

- protect the product in this container from excessive heat and direct sun.

Inactive Ingredients

WATER (AQUA), GLYCERIN, BUTYLOCTYL SALICYLATE, C12-15 ALKYL BENZOATE, SILICA, PONGAMIA GLABRA SEED OIL, UNDECANE, SODIUM HYALURONATE, GLYCINE SOJA (SOYBEAN) SEED EXTRACT, GLYCINE SOJA (SOYBEAN) OIL, PYRUS MALUS (APPLE) FRUIT EXTRACT, PONGAMIA PINNATA SEED EXTRACT, TOCOPHEROL, ORYZA SATIVA (RICE) GERM EXTRACT, ORYZA SATIVA (RICE) EXTRACT, TETRAHEXYLDECYL ASCORBATE, DUNALIELLA SALINA EXTRACT, HAEMATOCOCCUS PLUVIALIS EXTRACT, CAESALPINIA SPINOSA FRUIT POD EXTRACT, HELIANTHUS ANNUUS (SUNFLOWER) SPROUT EXTRACT, FRUCTOSE, GLUCOSE, TRIDECANE, ETHYL FERULATE, POLYGLYCERYL-4 LAURATE, HYDROXYETHYL ACRYLATE/SODIUM ACRYLOYLDIMETHYL TAURATE COPOLYMER, HYDROXYACETOPHENONE, POLYGLYCERYL-6 LAURATE, ARACHIDYL ALCOHOL, CELLULOSE GUM, POLYGLYCERYL-3 DIISOSTEARATE, BEHENYL ALCOHOL, SODIUM PHYTATE, ARACHIDYL GLUCOSIDE, MALTODEXTRIN, SODIUM DILAURAMIDOGLUTAMIDE LYSINE, POLYSORBATE 60, SORBITAN ISOSTEARATE, INULIN, XANTHAN GUM, CELLULOSE, PHENOXYETHANOL, CITRIC ACID

Questions or comments?

1-888-426-0695
Monday-Friday, 9 a.m. - 5 p.m. EST